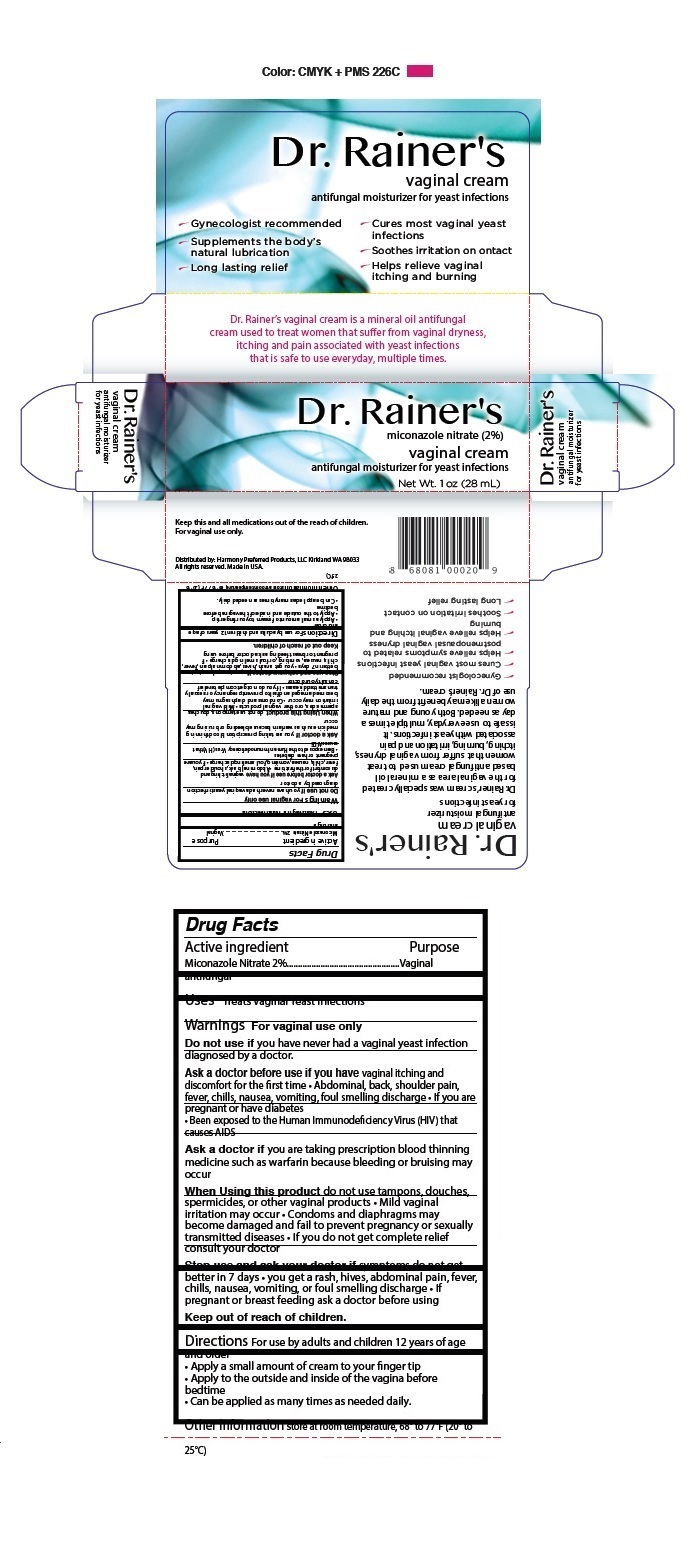 DRUG LABEL: Dr. Rainer s Vaginal Cream
NDC: 73736-115 | Form: CREAM
Manufacturer: Plexoris Health Care Products, Llc
Category: otc | Type: HUMAN OTC DRUG LABEL
Date: 20241211

ACTIVE INGREDIENTS: MICONAZOLE NITRATE 2 g/100 mL
INACTIVE INGREDIENTS: CARBOMER INTERPOLYMER TYPE A (ALLYL SUCROSE CROSSLINKED); AMINOMETHYLPROPANOL; ETHYLHEXYLGLYCERIN; GLYCOL STEARATE; MINERAL OIL; PEG-100 STEARATE; PHENOXYETHANOL; PROPYLENE GLYCOL; STEARIC ACID; STEARYL ALCOHOL; WATER

Dr. Rainer's Vaginal Cream

Active ingredient

Miconazole Nitrate 2%

Purpose

Vaginal antifungal

INDICATIONS AND USAGE

Uses Treats Vaginal Yeast Infections

Warnings

For vaginal use only
Do not use if you have never had a vaginal yeast infection diagnosed by a doctor.
Ask a doctor before use if you have vaginal itching and discomfort for the first time • Abdominal, back, shoulder pain, fever, chills, nausea, vomiting, foul smelling discharge • If you are pregnant or have diabetes
• Been exposed to the Human Immunodeficiency Virus (HIV) that causes AIDS
Ask a doctor if you are taking prescription blood thinning medicine such as warfarin because bleeding or bruising may occur
When Using this product do not use tampons, douches, spermicides, or other vaginal products • Mild vaginal irritation may occur • Condoms and diaphragms may become damaged and fail to prevent pregnancy or sexually transmitted diseases • If you do not get complete relief
consult your doctor
Stop use and ask your doctor if symptoms do not get better in 7 days • you get a rash, hives, abdominal pain, fever, chills, nausea, vomiting, or foul smelling discharge • If pregnant or breast feeding ask a doctor before using

Keep out of reach of children.

DOSAGE AND ADMINISTRATION

Directions For use by adults and children 12 years of age and older
• Apply a small amount of cream to your finger tip
• Apply to the outside and inside of the vagina before bedtime
• Can be applied as many times as needed daily.

Other information store at room temperature, 68° to 77°F (20° to 25°C)

INACTIVE INGREDIENT

Inactive ingredients Acrylates/C10-30 Alkyl Acrylate Crosspolymer, Aminomethyl Propanol, Ethylhexylglycerin, Glycol Stearate, Mineral Oil, PEG-100 Stearate, Phenoxyethanol, Propylene Glycol, Stearic Acid, Stearyl Alcohol, Water

antifungal moisturizer for yeast infections

- Gynecologist recommended
- Supplements the body’s natural lubrication
- Long lasting relief
- Cures most vaginal yeast infections
- Soothes irritation on ontact
- Helps relieve vaginal itching and burning

Dr. Rainer’s vaginal cream is a mineral oil antifungal cream used to treat women that suffer from vaginal dryness, itching and pain associated with yeast infections that is safe to use everyday, multiple times.

Keep this and all medications out of the reach of children.
For vaginal use only.

Distributed by: Harmony Preferred Products, LLC Kirkland WA 98033

All rights reserved. Made in USA.

Dr. Rainer’s cream was specially created for the vaginal area as a mineral oil based antifungal cream used to treat women that suffer from vaginal dryness, itching, burning, irritation and pain associated with yeast infections. It is safe to use everyday, multiple times a day as needed. Both young and mature women alike may benefit from the daily use of Dr. Rainer’s cream.